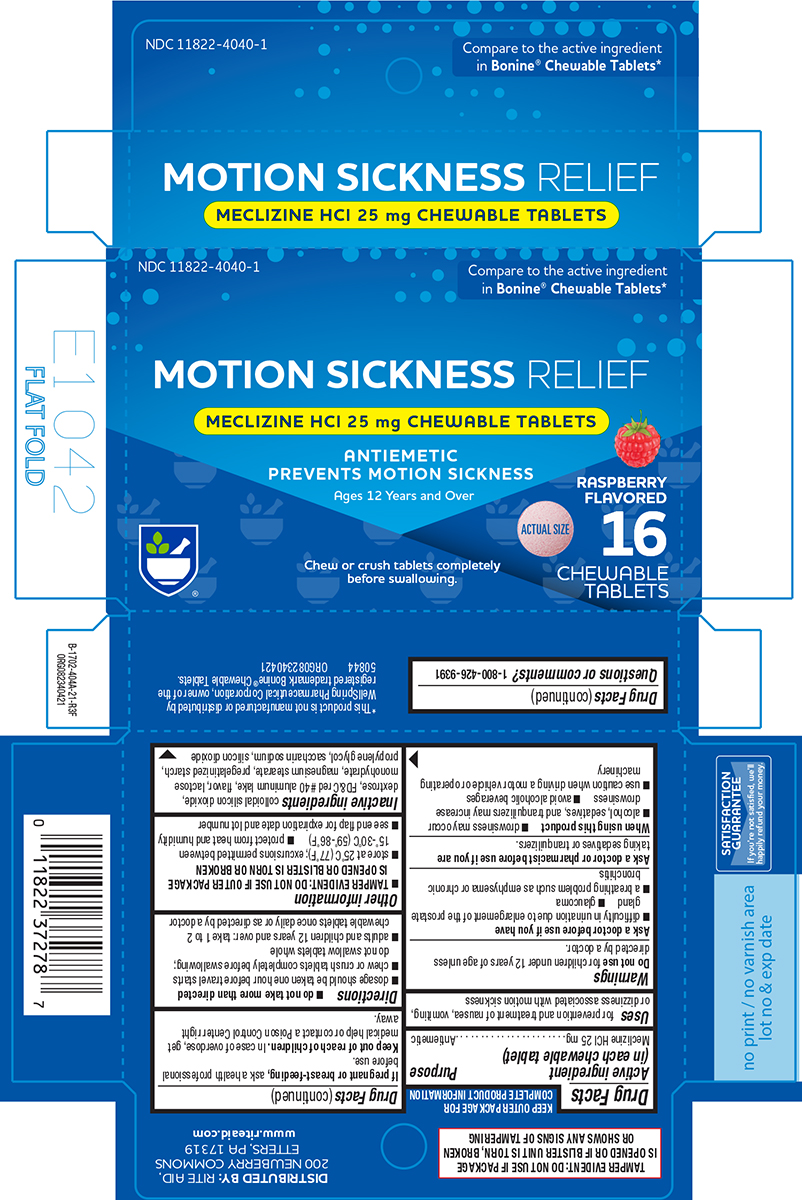 DRUG LABEL: Motion Sickness Relief
NDC: 11822-4040 | Form: TABLET, CHEWABLE
Manufacturer: Rite Aid Corporation
Category: otc | Type: HUMAN OTC DRUG LABEL
Date: 20251115

ACTIVE INGREDIENTS: MECLIZINE HYDROCHLORIDE 25 mg/1 1
INACTIVE INGREDIENTS: SILICON DIOXIDE; DEXTROSE, UNSPECIFIED FORM; FD&C RED NO. 40 ALUMINUM LAKE; LACTOSE MONOHYDRATE; MAGNESIUM STEARATE; STARCH, CORN; PROPYLENE GLYCOL; SACCHARIN SODIUM

Rite Aid 44-404A

Active ingredient (in each chewable tablet)

Meclizine HCl 25 mg

Purpose

Antiemetic

Uses

for prevention and treatment of nausea, vomiting, or dizziness associated with motion sickness

Warnings

Do not use

for children under 12 years of age unless directed by a doctor.

Ask a doctor before use if you have

- glaucoma
- difficulty in urination due to enlargement of the prostate gland
- a breathing problem such as emphysema or chronic bronchitis

Ask a doctor or pharmacist before use if you are

taking sedatives or tranquilizers.

When using this product

- drowsiness may occur
- alcohol, sedatives, and tranquilizers may increase drowsiness
- avoid alcoholic beverages
- use caution when driving a motor vehicle or operating machinery

If pregnant or breast-feeding,

ask a health professional before use.

Keep out of reach of children.

In case of overdose, get medical help or contact a Poison Control Center right away.

Directions

- do not take more than directed
- dosage should be taken one hour before travel starts
- chew or crush tablets completely before swallowing; do not swallow tablets whole
- adults and children 12 years and over: take 1 to 2 chewable tablets once daily or as directed by a doctor

Other information

- TAMPER EVIDENT: DO NOT USE IF OUTER PACKAGE IS OPENED OR BLISTER IS TORN OR BROKEN
- store at 25ºC (77ºF); excursions permitted between 15º-30ºC (59º-86ºF)
- protect from heat and humidity
- see end flap for expiration date and lot number

Inactive ingredients

colloidal silicon dioxide, dextrose, FD&C red #40 aluminum lake, flavor, lactose monohydrate, magnesium stearate, pregelatinized starch, propylene glycol, saccharin sodium, silicon dioxide

Questions or comments?

1-800-426-9391

Principal Display Panel

NDC 11822-4040-1

Compare to the active ingredient
in Bonine® Chewable Tablets*

MOTION SICKNESS RELIEF
MECLIZINE HCl 25 mg CHEWABLE TABLETS
ANTIEMETIC
PREVENTS MOTION SICKNESS
Ages 12 Years and Over

RASPBERRY
FLAVORED

16 CHEWABLE TABLETS

ACTUAL SIZE

Chew or crush tablets completely
before swallowing.

TAMPER EVIDENT: DO NOT USE IF PACKAGE
IS OPENED OR IF BLISTER UNIT IS TORN, BROKEN
OR SHOWS ANY SIGNS OF TAMPERING

*This product is not manufactured or distributed by
WellSpring Pharmaceutical Corporation, owner of the
registered trademark Bonine® Chewable Tablets.
50844 ORG082340421

DISTRIBUTED BY: RITE AID,
200 NEWBERRY COMMONS
ETTERS, PA 17319
www.riteaid.com

SATISFACTION
GUARANTEE
If you're not satisfied, we'll
happily refund your money.

Rite Aid 44-404A